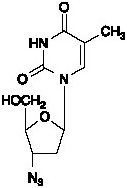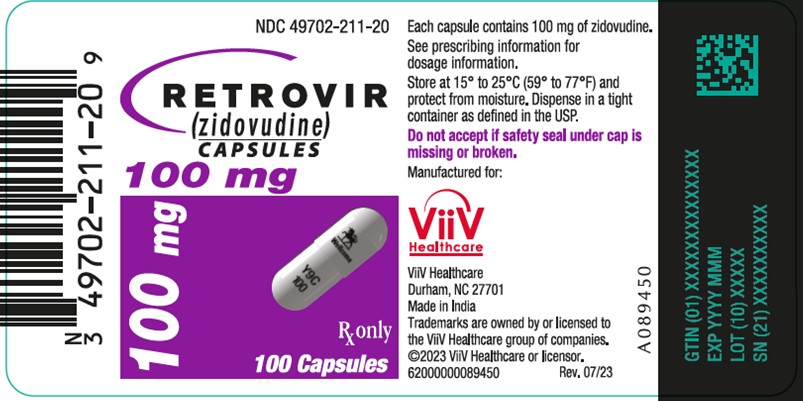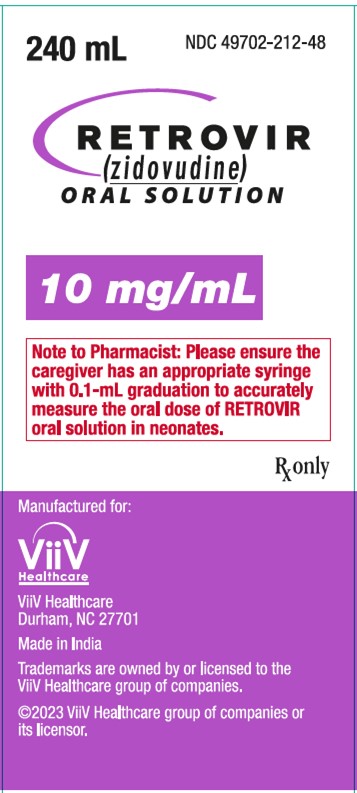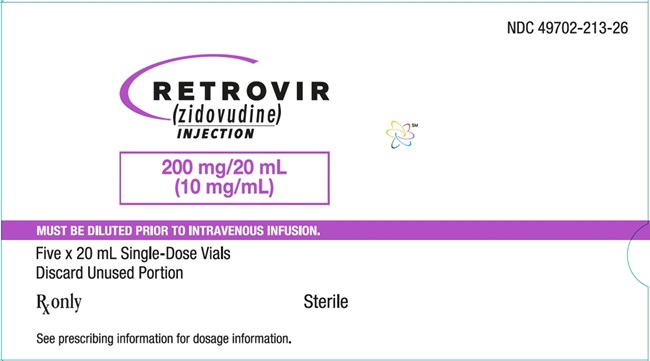 DRUG LABEL: RETROVIR
NDC: 49702-211 | Form: CAPSULE
Manufacturer: ViiV Healthcare Company
Category: prescription | Type: HUMAN PRESCRIPTION DRUG LABEL
Date: 20241113

ACTIVE INGREDIENTS: ZIDOVUDINE 100 mg/1 1
INACTIVE INGREDIENTS: STARCH, CORN; MAGNESIUM STEARATE; MICROCRYSTALLINE CELLULOSE; SODIUM STARCH GLYCOLATE TYPE A POTATO; FERROSOFERRIC OXIDE; DIMETHICONE, UNSPECIFIED; GELATIN, UNSPECIFIED; SHELLAC; SOYBEAN LECITHIN; TITANIUM DIOXIDE

HIGHLIGHTS OF PRESCRIBING INFORMATION

These highlights do not include all the information needed to use RETROVIR safely and effectively. See full prescribing information for RETROVIR.
RETROVIR (zidovudine) capsules, for oral use
RETROVIR (zidovudine) oral solution
RETROVIR (zidovudine) injection, for intravenous use
Initial U.S. Approval: 1987

WARNING: RISK OF HEMATOLOGICAL TOXICITY, MYOPATHY, LACTIC ACIDOSIS AND SEVERE HEPATOMEGALY WITH STEATOSIS

See full prescribing information for complete boxed warning.

- Hematologic toxicity including neutropenia and severe anemia have been associated with the use of zidovudine. (5.1)
- Symptomatic myopathy associated with prolonged use of zidovudine. (5.2)
- Lactic acidosis and severe hepatomegaly with steatosis, including fatal cases, have been reported with the use of nucleoside analogues including RETROVIR. Suspend treatment if clinical or laboratory findings suggestive of lactic acidosis or pronounced hepatotoxicity occur. (5.3)

1 INDICATIONS AND USAGE

RETROVIR is a nucleoside analogue reverse transcriptase inhibitor indicated for:

- Treatment of Human Immunodeficiency Virus (HIV-1) infection in combination with other antiretroviral agents. (1.1)
- Prevention of maternal-fetal HIV-1 transmission. (1.2)

2 DOSAGE AND ADMINISTRATION

- Treatment of HIV-1 infection:
Adults: Recommended oral dosage is 300 mg twice a day with other antiretroviral agents. For patients who are unable to take the oral formulations, the recommended intravenous dose is 1 mg per kg infused over 1 hour every 4 hours. (2.1)
Pediatric patients (aged 4 weeks to less than 18 years): Dosage should be calculated based on body weight not to exceed adult dose. (2.2)
- Prevention of maternal-fetal HIV-1 transmission:
Specific dosage instructions for mother and infant. (2.3)
- Patients with severe anemia and/or neutropenia:
Dosage interruption may be necessary. (2.4)
- Renal impairment: Recommended oral dosage in hemodialysis or peritoneal dialysis or in patients with creatinine clearance (CrCl) less than 15 mL per minute is 100 mg every 6 to 8 hours. Equivalent intravenous dosing is approximately 1 mg per kg every 6 to 8 hours. (2.5)

3 DOSAGE FORMS AND STRENGTHS

- Capsules: 100 mg (3)
- Oral Solution: 10 mg per mL (3)
- Injection: (10 mg per mL) 20-mL single-use vial (3)

4 CONTRAINDICATIONS

Hypersensitivity to zidovudine or any of the components (e.g., anaphylaxis, Stevens-Johnson syndrome). (4)

5 WARNINGS AND PRECAUTIONS

- See boxed warning for information about the following: hematologic toxicity, myopathy, and lactic acidosis and severe hepatomegaly. (5.1, 5.2, 5.3)
- Exacerbation of anemia has been reported in HIV-1/HCV co-infected patients receiving ribavirin and zidovudine. Coadministration of ribavirin and zidovudine is not advised. (5.4)
- Hepatic decompensation (some fatal) has occurred in HIV-1/HCV co-infected patients receiving combination antiretroviral therapy and interferon alfa with/without ribavirin. Discontinue RETROVIR as medically appropriate and consider dose reduction or discontinuation of interferon alfa, ribavirin, or both. (5.4)
- Immune reconstitution syndrome (5.5) and lipoatrophy (5.6) have been reported in patients treated with combination antiretroviral therapy.

6 ADVERSE REACTIONS

- Most commonly reported adverse reactions (incidence greater than or equal to 15%) in adult HIV-1 clinical trials were headache, malaise, nausea, anorexia, and vomiting. (6.1)
- Most commonly reported adverse reactions (incidence greater than or equal to 15%) in pediatric HIV-1 clinical trials were fever and cough. (6.1)
- Most commonly reported adverse reactions in neonates (incidence greater than or equal to 15%) in the prevention of maternal-fetal transmission of HIV-1 clinical trial were anemia and neutropenia. (6.1)

To report SUSPECTED ADVERSE REACTIONS, contact ViiV Healthcare at 1-877-844-8872 or FDA at 1-800-FDA-1088 or www.fda.gov/medwatch.

7 DRUG INTERACTIONS

- Avoid use with stavudine. (7.1)
- Avoid use with doxorubicin. (7.2)
- Bone marrow suppressive/cytotoxic agents: May increase the hematologic toxicity of zidovudine. (7.3)

8 USE IN SPECIFIC POPULATIONS

- Lactation: Women infected with HIV should be instructed not to breastfeed due to potential for HIV transmission. (8.2)

FULL PRESCRIBING INFORMATION

WARNING: RISK OF HEMATOLOGICAL TOXICITY, MYOPATHY, LACTIC ACIDOSIS AND SEVERE HEPATOMEGALY WITH STEATOSIS

RETROVIR (zidovudine) capsules, oral solution, and injection have been associated with hematologic toxicity including neutropenia and severe anemia, particularly in patients with advanced HIV-1 disease [see Warnings and Precautions (5.1)].

Prolonged use of RETROVIR has been associated with symptomatic myopathy [see Warnings and Precautions (5.2)].

Lactic acidosis and severe hepatomegaly with steatosis, including fatal cases, have been reported with the use of nucleoside analogues alone or in combination, including RETROVIR and other antiretrovirals. Suspend treatment if clinical or laboratory findings suggestive of lactic acidosis or pronounced hepatotoxicity occur [see Warnings and Precautions (5.3)].

1 INDICATIONS AND USAGE

1.1 Treatment of HIV-1

RETROVIR, a nucleoside reverse transcriptase inhibitor, is indicated in combination with other antiretroviral agents for the treatment of HIV-1 infection.

1.2 Prevention of Maternal-Fetal HIV-1 Transmission

RETROVIR is indicated for the prevention of maternal-fetal HIV-1 transmission [see Dosage and Administration (2.3)]. The indication is based on a dosing regimen that included 3 components:

1. antepartum therapy of HIV‑1–infected mothers
2. intrapartum therapy of HIV‑1–infected mothers
3. post-partum therapy of HIV‑1–exposed neonate

Points to consider prior to initiating RETROVIR in pregnant women for the prevention of maternal-fetal HIV-1 transmission include:

- In most cases, RETROVIR for prevention of maternal-fetal HIV-1 transmission should be given in combination with other antiretroviral drugs.
- Prevention of HIV-1 transmission in women who have received RETROVIR for a prolonged period before pregnancy has not been evaluated.
- Because the fetus is most susceptible to the potential teratogenic effects of drugs during the first 10 weeks of gestation and the risks of therapy with RETROVIR during that period are not fully known, women in the first trimester of pregnancy who do not require immediate initiation of antiretroviral therapy for their own health may consider delaying use; this indication is based on use after 14 weeks’ gestation.

2 DOSAGE AND ADMINISTRATION

2.1 Adults – Treatment of HIV-1 Infection

Oral Dosing

The recommended oral dose of RETROVIR is 300 mg twice daily in combination with other antiretroviral agents.

Intravenous (IV) Dosing

The recommended intravenous dose is 1 mg per kg infused at a constant rate over 1 hour every 4 hours. Patients should receive RETROVIR injection only until oral therapy can be administered.

- RETROVIR injection must be diluted prior to administration. The calculated dose should be removed from the 20-mL vial and added to 5% Dextrose injection solution to achieve a concentration no greater than 4 mg per mL.
- After dilution, the solution is physically and chemically stable for 24 hours at room temperature and 48 hours if refrigerated at 2°C to 8°C (36°F to 46°F). As an additional precaution, the diluted solution should be administered within 8 hours if stored at 25°C (77°F) or 24 hours if refrigerated at 2°C to 8°C to minimize potential administration of a microbially contaminated solution.
- Parenteral drug products should be inspected visually for particulate matter and discoloration prior to administration whenever solution and container permit and discarded if either is observed.
- Rapid infusion or bolus injection should be avoided. RETROVIR injection should not be given intramuscularly.

2.2 Pediatric Patients (Aged 4 Weeks to Less than 18 Years)

Healthcare professionals should pay special attention to accurate calculation of the dose of RETROVIR, transcription of the medication order, dispensing information, and dosing instructions to minimize risk for medication dosing errors.

Prescribers should calculate the appropriate dose of RETROVIR for each child based on body weight (kg) and should not exceed the recommended adult dose.

Before prescribing RETROVIR capsules, children should be assessed for the ability to swallow capsules. If a child is unable to reliably swallow a RETROVIR capsule, the RETROVIR oral solution formulation should be prescribed.

The recommended oral dosage in pediatric patients aged 4 weeks to less than 18 years and weighing greater than or equal to 4 kg is provided in Table 1. RETROVIR oral solution should be used to provide accurate dosage when capsules are not appropriate.

Table 1. Recommended Pediatric Oral Dosage of RETROVIR
Body Weight; (kg) | Total Daily Dose | Dosage Regimen and Dose
Body Weight; (kg) | Total Daily Dose | Twice Daily | Three Times Daily
4 to <9 | 24 mg/kg/day | 12 mg/kg | 8 mg/kg
≥9 to <30 | 18 mg/kg/day | 9 mg/kg | 6 mg/kg
≥30 | 600 mg/day | 300 mg | 200 mg

Alternatively, dosing for RETROVIR can be based on body surface area (BSA) for each child. The recommended oral dose of RETROVIR is 480 mg per m^2 per day in divided doses (240 mg per m^2 twice daily or 160 mg per m^2 three times daily). In some cases the dose calculated by mg per kg will not be the same as that calculated by BSA.

2.3 Prevention of Maternal-Fetal HIV-1 Transmission

The recommended dosage regimen for administration to pregnant women (greater than 14 weeks of pregnancy) and their neonates is:

Maternal Dosing

100 mg orally 5 times per day until the start of labor [see Clinical Studies (14.3)]. During labor and delivery, intravenous RETROVIR should be administered at 2 mg per kg (total body weight) over 1 hour followed by a continuous intravenous infusion of 1 mg per kg per hour (total body weight) until clamping of the umbilical cord.

Neonatal Dosing

Start neonatal dosing within 12 hours after birth and continue through 6 weeks of age. Neonates unable to receive oral dosing may be administered RETROVIR intravenously. See Table 2 for dosing recommendations.

Table 2. Recommended Neonatal Dosages of RETROVIR
Route | Total Daily Dose | Dose and Dosage Regimen
Oral | 8 mg/kg/day | 2 mg/kg every 6 hours
Intravenous | 6 mg/kg/day | 1.5 mg/kg infused over 30 minutes, every 6 hours

Use an appropriate-sized syringe with 0.1-mL graduation to ensure accurate dosing of the oral solution formulation in neonates.

2.4 Patients with Severe Anemia and/or Neutropenia

Significant anemia (hemoglobin less than 7.5 g per dL or reduction greater than 25% of baseline) and/or significant neutropenia (granulocyte count less than 750 cells per mm^3 or reduction greater than 50% from baseline) may require a dose interruption until evidence of marrow recovery is observed [see Warnings and Precautions (5.1)]. In patients who develop significant anemia, dose interruption does not necessarily eliminate the need for transfusion. If marrow recovery occurs following dose interruption, resumption in dose may be appropriate using adjunctive measures such as epoetin alfa at recommended doses, depending on hematologic indices such as serum erythropoietin level and patient tolerance.

2.5 Patients with Renal Impairment

In patients maintained on hemodialysis or peritoneal dialysis or with creatinine clearance (CrCl) by Cockcroft-Gault less than 15 mL per min, the recommended oral dosage is 100 mg every 6 to 8 hours. The intravenous dosing regimen equivalent to the oral administration of 100 mg every 6 to 8 hours is approximately 1 mg per kg every 6 to 8 hours [see Use in Specific Populations (8.6), Clinical Pharmacology (12.3)].

2.6 Patients with Hepatic Impairment

There are insufficient data to recommend dose adjustment of RETROVIR in patients with impaired hepatic function or liver cirrhosis. Frequent monitoring of hematologic toxicities is advised [see Use in Specific Populations (8.7)].

3 DOSAGE FORMS AND STRENGTHS

- RETROVIR capsules 100 mg (white, opaque cap and body) containing 100 mg zidovudine and printed with “Wellcome” and unicorn logo on cap and “Y9C” and “100” on body.
- RETROVIR oral solution (colorless to pale yellow, strawberry‑flavored) containing 10 mg zidovudine in each mL.
- RETROVIR injection is a clear, nearly colorless, sterile aqueous solution with a pH of approximately 5.5. Each vial contains 200 mg of zidovudine in 20 mL solution (10 mg per mL).

4 CONTRAINDICATIONS

RETROVIR is contraindicated in patients who have had a potentially life-threatening hypersensitivity reaction (e.g., anaphylaxis, Stevens-Johnson syndrome) to any of the components of the formulations.

5 WARNINGS AND PRECAUTIONS

5.1 Hematologic Toxicity/Bone Marrow Suppression

RETROVIR should be used with caution in patients who have bone marrow compromise evidenced by granulocyte count less than 1,000 cells per mm^3 or hemoglobin less than 9.5 g per dL. Hematologic toxicities appear to be related to pretreatment bone marrow reserve and to dose and duration of therapy. In patients with advanced symptomatic HIV-1 disease, anemia and neutropenia were the most significant adverse events observed. In patients who experience hematologic toxicity, a reduction in hemoglobin may occur as early as 2 to 4 weeks, and neutropenia usually occurs after 6 to 8 weeks. There have been reports of pancytopenia associated with the use of RETROVIR, which was reversible in most instances after discontinuance of the drug. However, significant anemia, in many cases requiring dose adjustment, discontinuation of RETROVIR, and/or blood transfusions, has occurred during treatment with RETROVIR alone or in combination with other antiretrovirals.

Frequent blood counts are strongly recommended to detect severe anemia or neutropenia in patients with poor bone marrow reserve, particularly in patients with advanced HIV-1 disease who are treated with RETROVIR. For HIV-1-infected individuals and patients with asymptomatic or early HIV-1 disease, periodic blood counts are recommended. If anemia or neutropenia develops, dosage interruption may be needed [see Dosage and Administration (2.4)].

5.2 Myopathy

Myopathy and myositis with pathological changes, similar to that produced by HIV-1 disease, have been associated with prolonged use of RETROVIR.

5.3 Lactic Acidosis and Severe Hepatomegaly with Steatosis

Lactic acidosis and severe hepatomegaly with steatosis, including fatal cases, have been reported with the use of nucleoside analogues, including zidovudine. A majority of these cases have been in women. Female sex and obesity may be risk factors for the development of lactic acidosis and severe hepatomegaly with steatosis in patients treated with antiretroviral nucleoside analogues. Treatment with RETROVIR should be suspended in any patient who develops clinical or laboratory findings suggestive of lactic acidosis or pronounced hepatotoxicity, which may include hepatomegaly and steatosis even in the absence of marked transaminase elevations.

5.4 Use with Interferon- and Ribavirin-Based Regimens in HIV-1/HCV Co-infected Patients

In vitro studies have shown ribavirin can reduce the phosphorylation of pyrimidine nucleoside analogues such as zidovudine. Although no evidence of a pharmacokinetic or pharmacodynamic interaction (e.g., loss of HIV-1/HCV virologic suppression) was seen when ribavirin was coadministered with zidovudine in HIV-1/HCV co-infected subjects [see Clinical Pharmacology (12.3)], exacerbation of anemia due to ribavirin has been reported when zidovudine is part of the HIV regimen. Coadministration of ribavirin and zidovudine is not advised. Consideration should be given to replacing zidovudine in established combination HIV-1/HCV therapy, especially in patients with a known history of zidovudine-induced anemia.

Hepatic decompensation (some fatal) has occurred in HIV-1/HCV co-infected patients receiving combination antiretroviral therapy for HIV-1 and interferon alfa with or without ribavirin. Patients receiving interferon alfa with or without ribavirin and RETROVIR should be closely monitored for treatment-associated toxicities, especially hepatic decompensation, neutropenia, and anemia.

Discontinuation of RETROVIR should be considered as medically appropriate. Dose reduction or discontinuation of interferon alfa, ribavirin, or both should also be considered if worsening clinical toxicities are observed, including hepatic decompensation (e.g., Child-Pugh greater than 6). See the full prescribing information for interferon and ribavirin.

5.5 Immune Reconstitution Syndrome

Immune reconstitution syndrome has been reported in patients treated with combination antiretroviral therapy, including RETROVIR. During the initial phase of combination antiretroviral treatment, patients whose immune systems respond may develop an inflammatory response to indolent or residual opportunistic infections (such as Mycobacterium avium infection, cytomegalovirus, Pneumocystis jirovecii pneumonia [PCP], or tuberculosis), which may necessitate further evaluation and treatment.

Autoimmune disorders (such as Graves’ disease, polymyositis, and Guillain-Barré syndrome) have also been reported to occur in the setting of immune reconstitution; however, the time to onset is more variable, and can occur many months after initiation of treatment.

5.6 Lipoatrophy

Treatment with zidovudine has been associated with loss of subcutaneous fat. The incidence and severity of lipoatrophy are related to cumulative exposure. This fat loss, which is most evident in the face, limbs, and buttocks, may be only partially reversible and improvement may take months to years after switching to a non-zidovudine-containing regimen. Patients should be regularly assessed for signs of lipoatrophy during therapy with zidovudine and other zidovudine-containing products, and if feasible, therapy should be switched to an alternative regimen if there is suspicion of lipoatrophy.

6 ADVERSE REACTIONS

The following adverse reactions are discussed in greater detail in other sections of the labeling:

- Hematologic toxicity, including neutropenia and anemia [see Boxed Warning, Warnings and Precautions (5.1)].
- Symptomatic myopathy [see Boxed Warning, Warnings and Precautions (5.2)].
- Lactic acidosis and severe hepatomegaly with steatosis [see Boxed Warning, Warnings and Precautions (5.3)].
- Hepatic decompensation in patients co-infected with HIV-1 and hepatitis C [see Warnings and Precautions (5.4)].

6.1 Clinical Trials Experience

Because clinical trials are conducted under widely varying conditions, adverse reaction rates observed in the clinical trials of a drug cannot be directly compared with rates in the clinical trials of another drug and may not reflect the rates observed in practice.

Adults

The frequency and severity of adverse reactions associated with the use of RETROVIR are greater in patients with more advanced infection at the time of initiation of therapy.

Table 3 summarizes adverse reactions reported at a statistically significant greater incidence for subjects receiving oral RETROVIR in a monotherapy trial.

Table 3. Percentage (%) of Subjects with Adverse Reactions (Greater than or Equal to 5% Frequency) in Asymptomatic HIV-1 Infection (ACTG 019)
Adverse Reaction | RETROVIR 500 mg/day; (n = 453) | Placebo; (n = 428)
Body as a whole
Asthenia | 9%a | 6%
Headache | 63% | 53%
Malaise | 53% | 45%
Gastrointestinal
Anorexia | 20% | 11%
Constipation | 6%a | 4%
Nausea | 51% | 30%
Vomiting | 17% | 10%
a Not statistically significant versus placebo.

In addition to the adverse reactions listed in Table 3, adverse reactions observed at an incidence of greater than or equal to 5% in any treatment arm in clinical trials (NUCA3001, NUCA3002, NUCB3001, and NUCB3002) were abdominal cramps, abdominal pain, arthralgia, chills, dyspepsia, fatigue, insomnia, musculoskeletal pain, myalgia, and neuropathy. Additionally, in these trials hyperbilirubinemia was reported at an incidence of less than or equal to 0.8%.

Selected laboratory abnormalities observed during a clinical trial of monotherapy with oral RETROVIR are shown in Table 4.

Table 4. Frequencies of Selected (Grade 3/4) Laboratory Abnormalities in Subjects with Asymptomatic HIV-1 Infection (ACTG 019)
Test; (Abnormal Level) | RETROVIR 500 mg/day; (n = 453) | Placebo; (n = 428)
Anemia (Hgb <8 g/dL) | 1% | <1%
Granulocytopenia (<750 cells/mm^3) | 2% | 2%
Thrombocytopenia (platelets <50,000/mm^3) | 0% | <1%
ALT (>5 x ULN) | 3% | 3%
AST (>5 x ULN) | 1% | 2%
ULN = Upper limit of normal.

The adverse reactions reported during IV administration of RETROVIR injection are similar to those reported with oral administration; neutropenia and anemia were reported most frequently. Long-term IV administration beyond 2 to 4 weeks has not been studied in adults and may enhance hematologic adverse reactions. Local reaction, pain, and slight irritation during IV administration occur infrequently.

Pediatrics

The clinical adverse reactions reported among adult recipients of RETROVIR may also occur in pediatric patients.

Trial ACTG 300: Selected clinical adverse reactions and physical findings with a greater than or equal to 5% frequency during therapy with EPIVIR (lamivudine) oral suspension 4 mg per kg twice daily plus RETROVIR 160 mg per m^2 3 times daily compared with didanosine in therapy-naive (less than or equal to 56 days of antiretroviral therapy) pediatric subjects are listed in Table 5.

Table 5. Selected Clinical Adverse Reactions and Physical Findings (Greater than or Equal to 5% Frequency) in Pediatric Subjects in Trial ACTG 300
Adverse Reaction | EPIVIR plus RETROVIR; (n = 236) | Didanosine; (n = 235)
Body as a whole
Fever | 25% | 32%
Digestive
Hepatomegaly | 11% | 11%
Nausea & vomiting | 8% | 7%
Diarrhea | 8% | 6%
Stomatitis | 6% | 12%
Splenomegaly | 5% | 8%
Respiratory
Cough | 15% | 18%
Abnormal breath sounds/wheezing | 7% | 9%
Ear, Nose, and Throat
Signs or symptoms of earsa | 7% | 6%
Nasal discharge or congestion | 8% | 11%
Other
Skin rashes | 12% | 14%
Lymphadenopathy | 9% | 11%
a Includes pain, discharge, erythema, or swelling of an ear.

Selected laboratory abnormalities experienced by therapy-naive (less than or equal to 56 days of antiretroviral therapy) pediatric subjects are listed in Table 6.

Table 6. Frequencies of Selected (Grade 3/4) Laboratory Abnormalities in Pediatric Subjects in Trial ACTG 300
Test; (Abnormal Level) | EPIVIR plus RETROVIR | Didanosine
Neutropenia (ANC <400 cells/mm^3) | 8% | 3%
Anemia (Hgb <7.0 g/dL) | 4% | 2%
Thrombocytopenia (platelets <50,000/mm^3) | 1% | 3%
ALT (>10 x ULN) | 1% | 3%
AST (>10 x ULN) | 2% | 4%
Lipase (>2.5 x ULN) | 3% | 3%
Total amylase (>2.5 x ULN) | 3% | 3%
ULN = Upper limit of normal.
ANC = Absolute neutrophil count.

Macrocytosis was reported in the majority of pediatric subjects receiving RETROVIR 180 mg per m^2 every 6 hours in open-label trials. Additionally, adverse reactions reported at an incidence of less than 6% in these trials were congestive heart failure, decreased reflexes, ECG abnormality, edema, hematuria, left ventricular dilation, nervousness/irritability, and weight loss.

Use for the Prevention of Maternal-Fetal Transmission of HIV-1

In a randomized, double-blind, placebo-controlled trial in HIV-1-infected women and their neonates conducted to determine the utility of RETROVIR for the prevention of maternal-fetal HIV-1 transmission, RETROVIR oral solution at 2 mg per kg was administered every 6 hours for 6 weeks to neonates beginning within 12 hours following birth. The most commonly reported adverse reactions were anemia (hemoglobin less than 9.0 g per dL) and neutropenia (less than 1,000 cells per mm^3). Anemia occurred in 22% of the neonates who received RETROVIR and in 12% of the neonates who received placebo. The mean difference in hemoglobin values was less than 1.0 g per dL for neonates receiving RETROVIR compared with neonates receiving placebo. No neonates with anemia required transfusion and all hemoglobin values spontaneously returned to normal within 6 weeks after completion of therapy with RETROVIR. Neutropenia in neonates was reported with similar frequency in the group that received RETROVIR (21%) and in the group that received placebo (27%). The long-term consequences of in utero and infant exposure to RETROVIR are unknown.

6.2 Postmarketing Experience

The following adverse reactions have been identified during post-approval use of RETROVIR. Because these reactions are reported voluntarily from a population of unknown size, it is not always possible to reliably estimate their frequency or establish a causal relationship to drug exposure.

Body as a Whole

Back pain, chest pain, flu-like syndrome, generalized pain, redistribution/accumulation of body fat [see Warnings and Precautions (5.6)].

Cardiovascular

Cardiomyopathy, syncope.

Eye

Macular edema.

Gastrointestinal

Constipation, dysphagia, flatulence, oral mucosa pigmentation, mouth ulcer.

General

Sensitization reactions including anaphylaxis and angioedema, vasculitis.

Hematologic

Aplastic anemia, hemolytic anemia, leukopenia, lymphadenopathy, pancytopenia with marrow hypoplasia, pure red cell aplasia.

Hepatobiliary

Hepatitis, hepatomegaly with steatosis, jaundice, lactic acidosis, pancreatitis.

Musculoskeletal

Increased CPK, increased LDH, muscle spasm, myopathy and myositis with pathological changes (similar to that produced by HIV-1 disease), rhabdomyolysis, tremor.

Nervous

Anxiety, confusion, depression, dizziness, loss of mental acuity, mania, paresthesia, seizures, somnolence, vertigo.

Reproductive System and Breast

Gynecomastia.

Respiratory

Dyspnea, rhinitis, sinusitis.

Skin and Subcutaneous Tissue

Changes in skin and nail pigmentation, pruritus, Stevens-Johnson syndrome, toxic epidermal necrolysis, sweating, urticaria.

Special Senses

Amblyopia, hearing loss, photophobia, taste perversion.

Renal and Urinary

Urinary frequency, urinary hesitancy.

7 DRUG INTERACTIONS

7.1 Antiretroviral Agents

Stavudine

Concomitant use of zidovudine with stavudine should be avoided since an antagonistic relationship has been demonstrated in vitro.

Nucleoside Analogues Affecting DNA Replication

Some nucleoside analogues affecting DNA replication, such as ribavirin, antagonize the in vitro antiviral activity of RETROVIR against HIV-1; concomitant use of such drugs should be avoided.

7.2 Doxorubicin

Concomitant use of zidovudine with doxorubicin should be avoided since an antagonistic relationship has been demonstrated in vitro.

7.3 Hematologic/Bone Marrow Suppressive/Cytotoxic Agents

Coadministration of ganciclovir, interferon alfa, ribavirin, and other bone marrow suppressive or cytotoxic agents may increase the hematologic toxicity of zidovudine.

8 USE IN SPECIFIC POPULATIONS

8.1 Pregnancy

Pregnancy Exposure Registry

There is a pregnancy exposure registry that monitors pregnancy outcomes in women exposed to RETROVIR during pregnancy. Healthcare providers are encouraged to register patients by calling the Antiretroviral Pregnancy Registry (APR) at 1-800-258-4263.

Risk Summary

Available data from the APR show no difference in the overall risk of birth defects for zidovudine compared with the background rate for birth defects of 2.7% in the Metropolitan Atlanta Congenital Defects Program (MACDP) reference population (see Data). The APR uses the MACDP as the U.S. reference population for birth defects in the general population. The MACDP evaluates women and infants from a limited geographic area and does not include outcomes for births that occurred at less than 20 weeks’ gestation. The rate of miscarriage is not reported in the APR. The estimated background rate of miscarriage in clinically recognized pregnancies in the U.S. general population is 15% to 20%. The background risk for major birth defects and miscarriage for the indicated population is unknown.

Hyperlactatemia, which may be due to mitochondrial dysfunction, has been reported in infants with in utero exposure to zidovudine-containing products. These events were transient and asymptomatic in most cases. There have been few reports of developmental delay, seizures, and other neurological disease. However, a causal relationship between these events and exposure to zidovudine-containing products in utero or peri-partum has not been established (see Data).

In an animal reproduction study, administration of oral zidovudine to female rats prior to mating and throughout gestation resulted in embryotoxicity at doses that produced systemic exposure (AUC) approximately 33 times higher than exposure at the recommended clinical dose. However, no embryotoxicity was observed after oral administration of zidovudine to pregnant rats during organogenesis at doses that produced systemic exposure (AUC) approximately 117 times higher than exposures at the recommended clinical dose. Administration of oral zidovudine to pregnant rabbits during organogenesis resulted in embryotoxicity at doses that produced systemic exposure (AUC) approximately 108 times higher than exposure at the recommended clinical dose. However, no embryotoxicity was observed at doses that produced systemic exposure (AUC) approximately 23 times higher than exposures at the recommended clinical dose (see Data).

Data

Human Data: Based on prospective reports to the APR of over 13,000 exposures to zidovudine during pregnancy resulting in live births (including over 4,000 exposed in the first trimester), there was no difference between the overall risk of birth defects for zidovudine compared with the background birth defect rate of 2.7% in a U.S. reference population of the MACDP. The prevalence of birth defects in live births was 3.2% (95% CI: 2.7% to 3.8%) following first trimester exposure to zidovudine-containing regimens and 2.8% (95% CI: 2.5% to 3.2%) following second/third trimester exposure to zidovudine-containing regimens.

A randomized, double‑blind, placebo‑controlled trial was conducted in HIV‑1–infected pregnant women to determine the utility of RETROVIR for the prevention of maternal‑fetal HIV‑1‑transmission [see Clinical Studies (14.3)]. Zidovudine treatment during pregnancy reduced the rate of maternal-fetal HIV-1 transmission from 24.9% for infants born to placebo-treated mothers to 7.8% for infants born to mothers treated with zidovudine. There were no differences in pregnancy-related adverse events between the treatment groups. Of the 363 neonates that were evaluated, congenital abnormalities occurred with similar frequency between neonates born to mothers who received RETROVIR and neonates born to mothers who received placebo. The observed abnormalities included problems in embryogenesis (prior to 14 weeks) or were recognized on ultrasound before or immediately after initiation of study drug.

Zidovudine has been shown to cross the placenta and concentrations in neonatal plasma at birth were essentially equal to those in maternal plasma at delivery [see Clinical Pharmacology (12.3)]. There have been reports of mild, transient elevations in serum lactate levels, which may be due to mitochondrial dysfunction, in neonates and infants exposed in utero or peri-partum to zidovudine-containing products. There have been few reports of developmental delay, seizures, and other neurological disease. However, a causal relationship between these events and exposure to zidovudine-containing products in utero or peri-partum has not been established. The clinical relevance of transient elevations in serum lactate is unknown.

Animal Data: A study in pregnant rats (at 50, 150, or 450 mg per kg per day starting 26 days prior to mating through gestation to postnatal Day 21) showed increased fetal resorptions at doses that produced systemic exposures (AUC) approximately 33 times higher than exposure at the recommended daily human dose (300 mg twice daily). However, in an oral embryo-fetal development study in rats (at 125, 250, or 500 mg per kg per day on Gestation Days 6 through 15), no fetal resorptions were observed at doses that produced systemic exposure (AUC) approximately 117 times higher than exposures at the recommended daily human dose. An oral embryo-fetal development study in rabbits (at 75, 150, or 500 mg per kg per day on Gestation Day 6 through 18) showed increased fetal resorptions at the 500-mg-per-kg-per-day dose, which produced systemic exposures (AUC) approximately 108 times higher than exposure at the recommended daily human dose; however, no fetal resorptions were noted at doses up to 150 mg per kg per day, which produced systemic exposure (AUC) approximately 23 times higher than exposures at the recommended daily human dose. These oral embryo-fetal development studies in the rat and rabbit revealed no evidence of fetal malformations with zidovudine. In another developmental toxicity study, pregnant rats (dosed at 3,000 mg per kg per day from Days 6 through 15 of gestation) showed marked maternal toxicity and an increased incidence of fetal malformations at exposures greater than 300 times the recommended daily human dose based on AUC. However, there were no signs of fetal malformations at doses up to 600 mg per kg per day.

8.2 Lactation

Risk Summary

The Centers for Disease Control and Prevention recommends that HIV‑1‑infected mothers in the United States not breastfeed their infants to avoid risking postnatal transmission of HIV‑1 infection. Zidovudine is present in human milk. There is no information on the effects of zidovudine on the breastfed infant or the effects of the drug on milk production. Because of the potential for (1) HIV‑1 transmission (in HIV-negative infants), (2) developing viral resistance (in HIV-positive infants), and (3) adverse reactions in a breastfed infant instruct mothers not to breastfeed if they are receiving RETROVIR.

8.4 Pediatric Use

RETROVIR has been studied in HIV-1-infected pediatric subjects aged at least 6 weeks who had HIV-1-related symptoms or who were asymptomatic with abnormal laboratory values indicating significant HIV-1-related immunosuppression. RETROVIR has also been studied in neonates perinatally exposed to HIV-1 [see Dosage and Administration (2.2), Adverse Reactions (6.1), Clinical Pharmacology (12.3), Clinical Studies (14.2, 14.3)].

8.5 Geriatric Use

Clinical studies of RETROVIR did not include sufficient numbers of subjects aged 65 and over to determine whether they respond differently from younger subjects. Other reported clinical experience has not identified differences in responses between the elderly and younger patients. In general, dose selection for an elderly patient should be cautious, reflecting the greater frequency of decreased hepatic, renal, or cardiac function, and of concomitant disease or other drug therapy.

8.6 Renal Impairment

Unchanged zidovudine and its glucuronide metabolite (formed in the liver) are primarily eliminated from the body by renal excretion. In patients with severely impaired renal function (CrCl less than 15 mL per min), dosage reduction is recommended [see Dosage and Administration (2.5), Clinical Pharmacology (12.3)].

8.7 Hepatic Impairment

RETROVIR is primarily eliminated by hepatic metabolism and zidovudine concentrations appear to be increased in patients with impaired hepatic function, which may increase the risk of hematologic toxicity. Frequent monitoring of hematologic toxicities is advised. There are insufficient data to recommend dose adjustment of RETROVIR in patients with impaired hepatic function or liver cirrhosis [see Dosage and Administration (2.6), Clinical Pharmacology (12.3)].

10 OVERDOSAGE

Acute overdoses of zidovudine have been reported in pediatric patients and adults. These involved exposures up to 50 grams. No specific symptoms or signs have been identified following acute overdosage with zidovudine apart from those listed as adverse events such as fatigue, headache, vomiting, and occasional reports of hematological disturbances. Patients recovered without permanent sequelae. Hemodialysis and peritoneal dialysis appear to have a negligible effect on the removal of zidovudine while elimination of its primary metabolite, 3′-azido-3′-deoxy-5′-O-β-D-glucopyranuronosylthymidine (GZDV), is enhanced. If overdose occurs, the patient should be monitored for evidence of toxicity and given standard supportive treatment as required.

11 DESCRIPTION

RETROVIR is the brand name for zidovudine (formerly called azidothymidine [AZT]), a pyrimidine nucleoside analogue active against HIV-1. The chemical name of zidovudine is 3′-azido-3′-deoxythymidine; it has the following structural formula:

Zidovudine is a white to beige, odorless, crystalline solid with a molecular weight of 267.24 and a solubility of 20.1 mg per mL in water at 25°C. The molecular formula is C10H13N5O4.

RETROVIR capsules are for oral administration. Each capsule contains 100 mg of zidovudine and the inactive ingredients corn starch, magnesium stearate, microcrystalline cellulose, and sodium starch glycolate. The 100-mg empty hard gelatin capsule, printed with edible black ink, consists of black iron oxide, dimethylpolysiloxane, gelatin, pharmaceutical shellac, soya lecithin, and titanium dioxide.

Each mL of RETROVIR oral solution contains 10 mg of zidovudine and the inactive ingredients sodium benzoate 0.2% (added as a preservative), citric acid, flavors, glycerin, and liquid sucrose. Sodium hydroxide may be added to adjust pH.

RETROVIR injection is a sterile solution for IV infusion only. Each mL contains 10 mg zidovudine in water for injection. Hydrochloric acid and/or sodium hydroxide may have been added to adjust the pH to approximately 5.5. RETROVIR injection contains no preservatives.

12 CLINICAL PHARMACOLOGY

12.1 Mechanism of Action

Zidovudine is an antiretroviral agent [see Microbiology (12.4)].

12.3 Pharmacokinetics

Absorption and Bioavailability

Following IV dosing, dose‑independent kinetics was observed over the range of 1 to 5 mg per kg. The mean steady‑state peak and trough concentrations of zidovudine at 2.5 mg per kg every 4 hours were 1.1 and 0.1 mcg per mL, respectively.

In adults, following oral administration, zidovudine is rapidly absorbed and extensively distributed, with peak serum concentrations occurring within 0.5 to 1.5 hours. The AUC was equivalent when zidovudine was administered as RETROVIR tablets or oral solution compared with RETROVIR capsules. The pharmacokinetic properties of zidovudine in fasting adult subjects are summarized in Table 7.

Table 7. Zidovudine Pharmacokinetic Parameters in Adult Subjects
Parameter | Mean ± SD; (except where noted)
Oral bioavailability (%) | 64 ± 10; (n = 5)
Apparent volume of distribution (L/kg) | 1.6 ± 0.6; (n = 8)
Cerebrospinal fluid (CSF):plasma ratioa | 0.6 [0.04 to 2.62]; (n = 39)
Systemic clearance (L/h/kg) | 1.6 ± 0.6; (n = 6)
Renal clearance (L/h/kg) | 0.34 ± 0.05; (n = 9)
Elimination half-life (h)b | 0.5 to 3; (n = 19)
a Median [range] for 50 paired samples drawn 1 to 8 hours after the last dose in subjects on chronic therapy with RETROVIR.
b Approximate range.

Distribution

The apparent volume of distribution of zidovudine is 1.6 ± 0.6 L per kg (Table 7) and binding to plasma protein is low (less than 38%).

Metabolism and Elimination

Zidovudine is primarily eliminated by hepatic metabolism. The major metabolite of zidovudine is GZDV. GZDV AUC is about 3-fold greater than the zidovudine AUC. Urinary recovery of zidovudine and GZDV accounts for 14% and 74%, respectively, of the dose following oral administration and 18% and 60%, respectively, following IV dosing. A second metabolite, 3′-amino-3′-deoxythymidine (AMT), has been identified in the plasma following single-dose IV administration of zidovudine. The AMT AUC was one-fifth of the zidovudine AUC. Pharmacokinetics of zidovudine were dose independent at oral dosing regimens ranging from 2 mg per kg every 8 hours to 10 mg per kg every 4 hours.

Effect of Food on Absorption

RETROVIR may be administered with or without food. The zidovudine AUC was similar when a single dose of zidovudine was administered with food.

Specific Populations

Patients with Renal Impairment: Zidovudine clearance was decreased resulting in increased zidovudine and GZDV half-life and AUC in subjects with impaired renal function (n = 14) following a single 200-mg oral dose (Table 8). Plasma concentrations of AMT were not determined. No dose adjustment is recommended for patients with CrCl greater than or equal to 15 mL per min.

Table 8. Zidovudine Pharmacokinetic Parameters in Subjects with Severe Renal Impairmenta
Parameter | Control Subjects; (Normal Renal Function); (n = 6) | Subjects with Renal Impairment; (n = 14)
CrCl (mL/min) | 120 ± 8 | 18 ± 2
Zidovudine AUC (ng•h/mL) | 1,400 ± 200 | 3,100 ± 300
Zidovudine half-life (h) | 1.0 ± 0.2 | 1.4 ± 0.1
a Data are expressed as mean ± standard deviation.

Hemodialysis and Peritoneal Dialysis: The pharmacokinetics and tolerance of zidovudine were evaluated in a multiple-dose trial in subjects undergoing hemodialysis (n = 5) or peritoneal dialysis (n = 6) receiving escalating oral doses up to 200 mg 5 times daily for 8 weeks. Daily doses of 500 mg or less were well tolerated despite significantly elevated GZDV plasma concentrations. Apparent zidovudine oral clearance was approximately 50% of that reported in subjects with normal renal function. Hemodialysis and peritoneal dialysis appeared to have a negligible effect on the removal of zidovudine, whereas GZDV elimination was enhanced. A dosage adjustment is recommended for patients undergoing hemodialysis or peritoneal dialysis [see Dosage and Administration (2.5)].

Patients with Hepatic Impairment: Data describing the effect of hepatic impairment on the pharmacokinetics of zidovudine are limited. However, zidovudine is eliminated primarily by hepatic metabolism and it appears that zidovudine clearance is decreased and plasma concentrations are increased in subjects with hepatic impairment. There are insufficient data to recommend dose adjustment of RETROVIR in patients with impaired hepatic function or liver cirrhosis [see Dosage and Administration (2.6)].

Pediatric Patients: Zidovudine pharmacokinetics have been evaluated in HIV-1-infected pediatric subjects (Table 9).

Patients Aged 3 Months to 12 Years: Overall, zidovudine pharmacokinetics in pediatric patients older than 3 months are similar to those in adult patients. Proportional increases in plasma zidovudine concentrations were observed following administration of oral solution from 90 to 240 mg per m^2 every 6 hours. Oral bioavailability, terminal half-life, and oral clearance were comparable to adult values. As in adult subjects, the major route of elimination was by metabolism to GZDV. After IV dosing, about 29% of the dose was excreted in the urine unchanged, and about 45% of the dose was excreted as GZDV [see Dosage and Administration (2.2)].

Patients Aged Less than 3 Months: Zidovudine pharmacokinetics have been evaluated in pediatric subjects from birth to 3 months of life. Zidovudine elimination was determined immediately following birth in 8 neonates who were exposed to zidovudine in utero. The half-life was 13.0 ± 5.8 hours. In neonates less than or equal to 14 days old, bioavailability was greater, total body clearance was slower, and half-life was longer than in pediatric subjects older than 14 days. For dose recommendations for neonates [see Dosage and Administration (2.3)].

Table 9. Zidovudine Pharmacokinetic Parameters in Pediatric Subjectsa
Parameter | Birth to 14 Days | Aged 14 Days to 3 Months | Aged 3 Months to 12 Years
Oral bioavailability (%) | 89 ± 19; (n = 15) | 61 ± 19; (n = 17) | 65 ± 24; (n = 18)
CSF:plasma ratio | no data | no data | 0.68 [0.03 to 3.25]b; (n = 38)
CL (L/h/kg) | 0.65 ± 0.29; (n = 18) | 1.14 ± 0.24; (n = 16) | 1.85 ± 0.47; (n = 20)
Elimination half-life (h) | 3.1 ± 1.2; (n = 21) | 1.9 ± 0.7; (n = 18) | 1.5 ± 0.7; (n = 21)
a Data presented as mean ± standard deviation except where noted.
b Median [range].

Pregnant Women: Zidovudine pharmacokinetics have been studied in a Phase I trial of 8 women during the last trimester of pregnancy. Zidovudine pharmacokinetics were similar to those of nonpregnant adults. Consistent with passive transmission of the drug across the placenta, zidovudine concentrations in neonatal plasma at birth were essentially equal to those in maternal plasma at delivery [see Use in Specific Populations (8.1)].

Although data are limited, methadone maintenance therapy in 5 pregnant women did not appear to alter zidovudine pharmacokinetics.

Geriatric Patients: Zidovudine pharmacokinetics have not been studied in subjects over 65 years of age.

Male and Female Patients: A pharmacokinetic trial in healthy male (n = 12) and female (n = 12) subjects showed no differences in zidovudine AUC when a single dose of zidovudine was administered as a 300-mg RETROVIR tablet.

Drug Interaction Studies

[See Drug Interactions (7).]

Table 10. Effect of Coadministered Drugs on Zidovudine AUCa
Note: ROUTINE DOSE MODIFICATION OF ZIDOVUDINE IS NOT WARRANTED WITH COADMINISTRATION OF THE FOLLOWING DRUGS.
Coadministered Drug and Dose | Zidovudine Oral Dose | n | Zidovudine Concentrations |  | Concentration of Coadministered Drug
Coadministered Drug and Dose | Zidovudine Oral Dose | n | AUC | Variability | Concentration of Coadministered Drug
Atovaquone; 750 mg every 12 h with food | 200 mg every 8 h | 14 | ↑31% | Range:; 23% to 78%b | ↔
Clarithromycin; 500 mg twice daily | 100 mg every 4 h x 7 days | 4 | ↓12% | Range:; ↓34% to ↑14%b | Not Reported
Fluconazole; 400 mg daily | 200 mg every 8 h | 12 | ↑74% | 95% CI:; 54% to 98% | Not Reported
Lamivudine; 300 mg every 12 h | single 200 mg | 12 | ↑13% | 90% CI:; 2% to 27% | ↔
Methadone; 30 to 90 mg daily | 200 mg every 4 h | 9 | ↑43% | Range:; 16% to 64%b | ↔
Nelfinavir; 750 mg every 8 h x 7 to 10 days | single 200 mg | 11 | ↓35% | Range:; 28% to 41%b | ↔
Probenecid; 500 mg every 6 h x 2 days | 2 mg/kg every 8 h x 3 days | 3 | ↑106% | Range:; 100% to 170%b | Not Assessed
Rifampin; 600 mg daily x 14 days | 200 mg every 8 h x 14 days | 8 | ↓47% | 90% CI:; 41% to 53% | Not Assessed
Ritonavir; 300 mg every 6 h x 4 days | 200 mg every 8 h x 4 days | 9 | ↓25% | 95% CI:; 15% to 34% | ↔
Valproic acid; 250 mg or 500 mg every 8 h x 4 days | 100 mg every 8 h x 4 days | 6 | ↑80% | Range:; 64% to 130%b | Not Assessed
↑ = Increase; ↓ = Decrease; ↔ = No significant change; AUC = Area under the concentration versus time curve; CI = Confidence interval.
a This table is not all inclusive.
b Estimated range of percent difference.

Phenytoin: Phenytoin plasma levels have been reported to be low in some patients receiving RETROVIR, while in one case a high level was documented. However, in a pharmacokinetic interaction trial in which 12 HIV-1-positive volunteers received a single 300-mg phenytoin dose alone and during steady-state zidovudine conditions (200 mg every 4 hours), no change in phenytoin kinetics was observed. Although not designed to optimally assess the effect of phenytoin on zidovudine kinetics, a 30% decrease in oral zidovudine clearance was observed with phenytoin.

Ribavirin: In vitro data indicate ribavirin reduces phosphorylation of lamivudine, stavudine, and zidovudine. However, no pharmacokinetic (e.g., plasma concentrations or intracellular triphosphorylated active metabolite concentrations) or pharmacodynamic (e.g., loss of HIV-1/HCV virologic suppression) interaction was observed when ribavirin and lamivudine (n = 18), stavudine (n = 10), or zidovudine (n = 6) were coadministered as part of a multi-drug regimen to HIV-1/HCV co-infected subjects [see Warnings and Precautions (5.4)].

12.4 Microbiology

Mechanism of Action

Zidovudine is a synthetic nucleoside analogue. Intracellularly, zidovudine is phosphorylated to its active 5′-triphosphate metabolite, zidovudine triphosphate (ZDV-TP). The principal mode of action of ZDV-TP is inhibition of reverse transcriptase (RT) via DNA chain termination after incorporation of the nucleotide analogue. ZDV-TP is a weak inhibitor of the cellular DNA polymerases α and γ and has been reported to be incorporated into the DNA of cells in culture.

Antiviral Activity

The antiviral activity of zidovudine against HIV-1 was assessed in a number of cell lines including monocytes and fresh human peripheral blood lymphocytes. The EC50 and EC90 values for zidovudine were 0.01 to 0.49 microM (1 microM = 0.27 mcg per mL) and 0.1 to 9 microM, respectively. HIV-1 from therapy-naive subjects with no amino acid substitutions associated with resistance gave median EC50 values of 0.011 microM (range: 0.005 to 0.110 microM) from Virco (n = 92 baseline samples) and 0.0017 microM (range: 0.006 to 0.0340 microM) from Monogram Biosciences (n = 135 baseline samples). The EC50 values of zidovudine against different HIV-1 clades (A-G) ranged from 0.00018 to 0.02 microM, and against HIV-2 isolates from 0.00049 to 0.004 microM. Zidovudine was not antagonistic to tested anti-HIV agents with the exception of stavudine where an antagonistic relationship with zidovudine has been demonstrated in cell culture. Ribavirin has been found to inhibit the phosphorylation of zidovudine in cell culture.

Resistance

HIV-1 isolates with reduced susceptibility to zidovudine have been selected in cell culture and were also recovered from subjects treated with zidovudine. Genotypic analyses of the isolates selected in cell culture and recovered from zidovudine‑treated subjects showed thymidine analog mutation (TAMs) substitutions in the HIV‑1 RT (M41L, D67N, K70R, L210W, T215Y or F, and K219E/R/H/Q/N/Q) that confer zidovudine resistance. In general, higher levels of resistance were associated with greater number of substitutions. In some subjects harboring zidovudine‑resistant virus at baseline, phenotypic sensitivity to zidovudine was restored by 12 weeks of treatment with lamivudine and zidovudine.

Cross-Resistance

Cross-resistance has been observed among NRTIs. TAM substitutions are selected by zidovudine and confer cross‑resistance to abacavir, didanosine, stavudine, and tenofovir.

13 NONCLINICAL TOXICOLOGY

13.1 Carcinogenesis, Mutagenesis, Impairment of Fertility

Carcinogenesis

Zidovudine was administered orally at 3 dosage levels to separate groups of mice and rats (60 females and 60 males in each group). Initial single daily doses were 30, 60, and 120 mg per kg per day in mice and 80, 220, and 600 mg per kg per day in rats. The doses in mice were reduced to 20, 30, and 40 mg per kg per day after Day 90 because of treatment-related anemia, whereas in rats only the high dose was reduced to 450 mg per kg per day on Day 91 and then to 300 mg per kg per day on Day 279.

In mice, 7 late-appearing (after 19 months) vaginal neoplasms (5 non-metastasizing squamous cell carcinomas, 1 squamous cell papilloma, and 1 squamous polyp) occurred in animals given the highest dose. One late-appearing squamous cell papilloma occurred in the vagina of a middle-dose animal. No vaginal tumors were found at the lowest dose.

In rats, 2 late-appearing (after 20 months), non-metastasizing vaginal squamous cell carcinomas occurred in animals given the highest dose. No vaginal tumors occurred at the low or middle dose in rats. No other drug-related tumors were observed in either sex of either species.

At doses that produced tumors in mice and rats, the estimated drug exposure (as measured by AUC) was approximately 3 times (mouse) and 24 times (rat) the estimated human exposure at the recommended therapeutic dose of 100 mg every 4 hours.

It is not known how predictive the results of rodent carcinogenicity studies may be for humans.

Two transplacental carcinogenicity studies were conducted in mice. One study administered zidovudine at doses of 20 mg per kg per day or 40 mg per kg per day from Gestation Day 10 through parturition and lactation with dosing continuing in offspring for 24 months postnatally. The doses of zidovudine administered in this study produced zidovudine exposures approximately 3 times the estimated human exposure at recommended doses. After 24 months, an increase in incidence of vaginal tumors was noted with no increase in tumors in the liver or lung or any other organ in either gender. These findings are consistent with results of the standard oral carcinogenicity study in mice, as described earlier. A second study administered zidovudine at maximum tolerated doses of 12.5 mg per day or 25 mg per day (approximately 1,000 mg per kg nonpregnant body weight or approximately 450 mg per kg of term body weight) to pregnant mice from Days 12 through 18 of gestation. There was an increase in the number of tumors in the lung, liver, and female reproductive tracts in the offspring of mice receiving the higher dose level of zidovudine.

Mutagenesis

Zidovudine was mutagenic in a 5178Y/TK+/- mouse lymphoma assay, positive in an in vitro cell transformation assay, clastogenic in a cytogenetic assay using cultured human lymphocytes, and positive in mouse and rat micronucleus tests after repeated doses. It was negative in a cytogenetic study in rats given a single dose.

Impairment of Fertility

Zidovudine, administered to male and female rats at doses up to 450 mg per kg per day, which is 7 times the recommended adult dose (300 mg twice daily) based on body surface area, had no effect on fertility based on conception rates.

14 CLINICAL STUDIES

Therapy with RETROVIR has been shown to prolong survival and decrease the incidence of opportunistic infections in patients with advanced HIV-1 disease and to delay disease progression in asymptomatic HIV-1-infected patients.

14.1 Adults

Combination Therapy

RETROVIR in combination with other antiretroviral agents has been shown to be superior to monotherapy for one or more of the following endpoints: delaying death, delaying development of AIDS, increasing CD4+ cell counts, and decreasing plasma HIV-1 RNA.

The clinical efficacy of a combination regimen that includes RETROVIR was demonstrated in trial ACTG 320. This trial was a multi-center, randomized, double-blind, placebo-controlled trial that compared RETROVIR 600 mg per day plus EPIVIR 300 mg per day with RETROVIR plus EPIVIR plus indinavir 800 mg three times daily. The incidence of AIDS-defining events or death was lower in the triple-drug–containing arm compared with the 2-drug–containing arm (6.1% versus 10.9%, respectively).

Monotherapy

In controlled trials of treatment-naive subjects conducted between 1986 and 1989, monotherapy with RETROVIR, as compared with placebo, reduced the risk of HIV-1 disease progression, as assessed using endpoints that included the occurrence of HIV-1-related illnesses, AIDS-defining events, or death. These trials enrolled subjects with advanced disease (BW 002), and asymptomatic or mildly symptomatic disease in subjects with CD4+ cell counts between 200 and 500 cells per mm^3 (ACTG 016 and ACTG 019). A survival benefit for monotherapy with RETROVIR was not demonstrated in the latter 2 trials. Subsequent trials showed that the clinical benefit of monotherapy with RETROVIR was time limited.

14.2 Pediatric Patients

ACTG 300 was a multi-center, randomized, double-blind trial that provided for comparison of EPIVIR plus RETROVIR to didanosine monotherapy. A total of 471 symptomatic, HIV-1-infected therapy-naive pediatric subjects were enrolled in these 2 treatment arms. The median age was 2.7 years (range: 6 weeks to 14 years), the mean baseline CD4+ cell count was 868 cells per mm^3, and the mean baseline plasma HIV-1 RNA was 5.0 log10 copies per mL. The median duration that subjects remained on trial was approximately 10 months. Results are summarized in Table 11.

Table 11. Number of Subjects (%) Reaching a Primary Clinical Endpoint (Disease Progression or Death)
Endpoint | EPIVIR plus RETROVIR; (n = 236) | Didanosine; (n = 235)
HIV disease progression or death (total) | 15 (6.4%) | 37 (15.7%)
Physical growth failure | 7 (3.0%) | 6 (2.6%)
Central nervous system deterioration | 4 (1.7%) | 12 (5.1%)
CDC Clinical Category C | 2 (0.8%) | 8 (3.4%)
Death | 2 (0.8%) | 11 (4.7%)

14.3 Prevention of Maternal-Fetal HIV-1 Transmission

The utility of RETROVIR for the prevention of maternal-fetal HIV-1 transmission was demonstrated in a randomized, double-blind, placebo-controlled trial (ACTG 076) conducted in HIV-1-infected pregnant women with CD4+ cell counts of 200 to 1,818 cells per mm^3 (median in the treated group: 560 cells per mm^3) who had little or no previous exposure to RETROVIR. Oral RETROVIR was initiated between 14 and 34 weeks of gestation (median 11 weeks of therapy) followed by IV administration of RETROVIR during labor and delivery. Following birth, neonates received RETROVIR oral solution for 6 weeks. The trial showed a statistically significant difference in the incidence of HIV-1 infection in the neonates (based on viral culture from peripheral blood) between the group receiving RETROVIR and the group receiving placebo. Of 363 neonates evaluated in the trial, the estimated risk of HIV-1 infection was 7.8% in the group receiving RETROVIR and 24.9% in the placebo group, a relative reduction in transmission risk of 68.7%. RETROVIR was well tolerated by mothers and infants. There was no difference in pregnancy-related adverse events between the treatment groups.

16 HOW SUPPLIED/STORAGE AND HANDLING

RETROVIR 100-mg capsules are supplied as white, opaque cap and body capsules containing 100 mg zidovudine per capsule. Each capsule is printed with “Wellcome” and unicorn logo on cap and “Y9C” and “100” on body.

Bottles of 100 (NDC 49702-211-20).

Store at 15° to 25°C (59° to 77°F) and protect from moisture.

RETROVIR oral solution is supplied as a colorless to pale yellow, strawberry-flavored solution containing 10 mg zidovudine in each mL.

Bottle of 240 mL (NDC 49702-212-48) with child-resistant cap.

Store at 15° to 25°C (59° to 77°F).

RETROVIR injection is a clear, colorless to slightly yellow aqueous solution. The strength of the presentation is 200 mg of zidovudine in 20 mL solution (10 mg per mL).

Single-dose vial (NDC 49702-213-01), Carton of 5 (NDC 49702-213-26).

Store vials at 15° to 25°C (59° to 77°F) and protect from light.

17 PATIENT COUNSELING INFORMATION

Hypersensitivity Reactions

Inform patients that potentially life‑threatening hypersensitivity reactions (e.g., anaphylaxis, Stevens-Johnson syndrome) can occur while receiving RETROVIR. Instruct patients to immediately contact their healthcare provider if they develop rash, as it may be a sign of a more serious reaction. Advise patients that it is very important that they remain under a healthcare provider’s care during treatment with RETROVIR [see Contraindications (4)].

Neutropenia and Anemia

Inform patients that the major toxicities of RETROVIR are neutropenia and/or anemia. The frequency and severity of these toxicities are greater in patients with more advanced disease and in those who initiate therapy later in the course of their infection. Advise patients that if toxicity develops, they may require transfusions or drug discontinuation. Advise patients of the extreme importance of having their blood counts followed closely while on therapy, especially for patients with advanced symptomatic HIV-1 disease [see Boxed Warning, Warnings and Precautions (5.1)].

Myopathy

Inform patients that myopathy and myositis with pathological changes, similar to that produced by HIV-1 disease, have been associated with prolonged use of RETROVIR [see Boxed Warning, Warnings and Precautions (5.2)].

Lactic Acidosis/Hepatomegaly with Steatosis

Advise patients that lactic acidosis and severe hepatomegaly with steatosis have been reported with use of nucleoside analogues and other antiretrovirals. Advise patients to stop taking RETROVIR if they develop clinical symptoms suggestive of lactic acidosis or pronounced hepatotoxicity [see Boxed Warning, Warnings and Precautions (5.3)].

HIV-1/HCV Co-infection

Inform patients with HIV-1/HCV co-infection that hepatic decompensation (some fatal) has occurred in HIV-1/HCV co-infected patients receiving combination antiretroviral therapy for HIV-1 and interferon alfa with or without ribavirin [see Warnings and Precautions (5.4)].

Immune Reconstitution Syndrome

Advise patients to inform their healthcare provider immediately of any signs and symptoms of infection as inflammation from previous infection may occur soon after combination antiretroviral therapy, including when RETROVIR is started [see Warnings and Precautions (5.5)].

Lipoatrophy

Advise patients that loss of subcutaneous fat may occur in patients receiving RETROVIR and that they will be regularly assessed during therapy [see Warnings and Precautions (5.6)].

Common Adverse Reactions

Inform patients that the most commonly reported adverse reactions in adult patients being treated with RETROVIR were headache, malaise, nausea, anorexia, and vomiting. The most commonly reported adverse reactions in pediatric patients receiving RETROVIR were fever, cough, and digestive disorders. Patients also should be encouraged to contact their physician if they experience muscle weakness, shortness of breath, symptoms of hepatitis or pancreatitis, or any other unexpected adverse events while being treated with RETROVIR [see Adverse Reactions (6)].

Drug Interactions

Advise patients that other medications may interact with RETROVIR and certain medications, including ganciclovir, interferon alfa, and ribavirin, may exacerbate the toxicity of RETROVIR [see Drug Interactions (7)].

Dosage and Administration in Neonates

Due to the small volume of RETROVIR administered to neonates, advise caregivers to use an appropriate-sized syringe with 0.1-mL graduation to ensure accurate dosing of the oral solution formulation [see Dosage and Administration (2.3)].

Pregnancy

Inform pregnant women considering the use of RETROVIR during pregnancy for prevention of HIV-1 transmission to their infants that transmission may still occur in some cases despite therapy.

Pregnancy Registry

Advise patients that there is a pregnancy exposure registry that monitors pregnancy outcomes in women exposed to RETROVIR during pregnancy [see Use in Specific Populations (8.1)].

Lactation

Instruct women with HIV-1 infection not to breastfeed because HIV-1 can be passed to the baby in the breast milk [see Use in Specific Populations (8.2)].

Missed Dose

Instruct patients that if they miss a dose of RETROVIR, to take it as soon as they remember. Advise patients not to double their next dose or take more than the prescribed dose [see Dosage and Administration (2)].

EPIVIR and RETROVIR are trademarks owned by or licensed to the ViiV Healthcare group of companies.

Manufactured for:

ViiV Healthcare

Durham, NC 27701

©2024 ViiV Healthcare group of companies or its licensor.

RTR:13PI

PACKAGE LABEL

PRINCIPAL DISPLAY PANEL

NDC 49702-211-20

RETROVIR

(zidovudine)

CAPSULES

100 mg

100 mg

Rx only

100 Capsules

Each capsule contains 100 mg of zidovudine.

See prescribing information for dosing information.

Store at 15o to 25oC (59o to 77oF) and protect from moisture. Dispense in a tight container as defined in the USP.

Do not accept if safety seal under cap is missing or broken.

Manufactured for:

ViiV Healthcare

Durham, NC 27701

Made in India

Trademarks owned or licensed by the ViiV Healthcare group of companies.

©2023 ViiV Healthcare or licensor.

Rev. 07/23

62000000089450

PACKAGE LABEL

PRINCIPAL DISPLAY PANEL

NDC 49702-212-48

RETROVIR

(zidovudine)

ORAL SOLUTION

10 mg/mL

240 mL

Note to Pharmacist: Please ensure the caregiver has an appropriate syringe with 0.1-mL graduation to accurately measure the oral dose of RETROVIR oral solution in neonates.

Rx only

Manufactured for:

ViiV Healthcare

Durham, NC 27701

Made in India

Trademarks are owned by or licensed to the ViiV Healthcare group of companies.

©2023 ViiV Healthcare group of companies or its licensor.

30000000001038 Rev. 7/23

PACKAGE LABEL

PRINCIPAL DISPLAY PANEL

NDC 49702-213-26

RETROVIR

(zidovudine)

INJECTION

200 mg/20 mL (10 mg/mL)

MUST BE DILUTED PRIOR TO INTRAVENOUS INFUSION.

Five x 20 mL Single-Dose Vials

Discard Unused Portion

Rx only

Sterile

Made in India

©2025 ViiV Healthcare group of companies or its licensor.

Trademark is owned by or licensed to the ViiV Healthcare group of companies.

62000000099203 Rev. 03/25